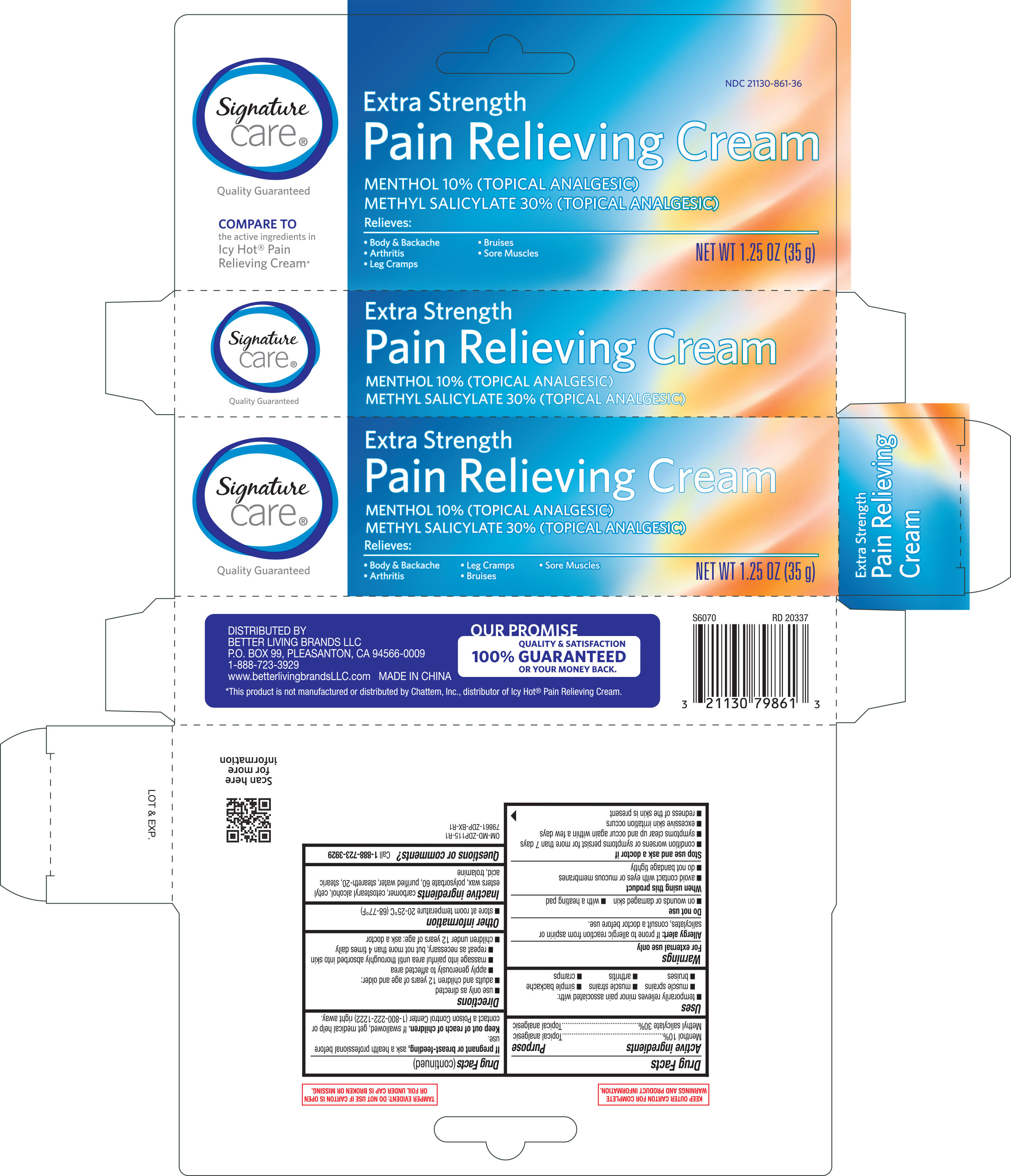 DRUG LABEL: Signature Care Cold and Hot
NDC: 21130-861 | Form: CREAM
Manufacturer: Safeway Inc.
Category: otc | Type: HUMAN OTC DRUG LABEL
Date: 20251024

ACTIVE INGREDIENTS: METHYL SALICYLATE 30 g/100 g; MENTHOL 10 g/100 g
INACTIVE INGREDIENTS: STEARIC ACID; CETYL ESTERS WAX; TROLAMINE; POLYSORBATE 60; WATER; STEARETH-20; CARBOMER HOMOPOLYMER, UNSPECIFIED TYPE; CETOSTEARYL ALCOHOL

Signature Care Cold & Hot Cream 1.25 oz 79861 ZDP (2021)

Active ingredients Purpose

Methol 10%........................................... Topical analgesic

Methyl Salicylate 30%........................... Topical analgesic

Uses

- temporarily relieves minor pain associated with:
- muscle sprains
- muscle strains
- simple backache
- bruises
- arthritis
- cramps

Warnings

For external use only

Allergy alert: if prone to allergic reaction from aspirin or salicylates, consult a doctor before use.

Do not use

- on wounds or damaged skin
- with a heating pad

When using this product

- avoid contact with eyes or mucous membranes
- do not bandage tightly

Stop use and ask a doctor if

- condition worsens or symptoms persist for more than 7 days
- symptoms clear up and occur again within a few days
- excessive skin irritation occurs
- redness of the skin is present

PREGNANCY OR BREAST FEEDING

If pregnant or breast-feeding, ask a health professional before use

Keep out of reach of children. If swallowed, get medical help or contact a Poison Control Center (1-800-222-1222) right away.

Directions

- use only as directed
- adults and children 12 years of age and older:
- apply generously to affected area
- massage into painful area until thoroughly absorbed into skin
- repeat as necessary, but not more than 4 times daily
- children under 12 years of age: ask a doctor

Other information

- store at room temperature 20-25°C (68-77°F)

Inactive ingredients

carbomer, cetostearyl alcohol, cetyl esters, polysorbate 60, purified water, steareth-20, stearic acid, trolamine

DOSAGE AND ADMINISTRATION

Distributed by:

Better Living Brands LLC

Made in China